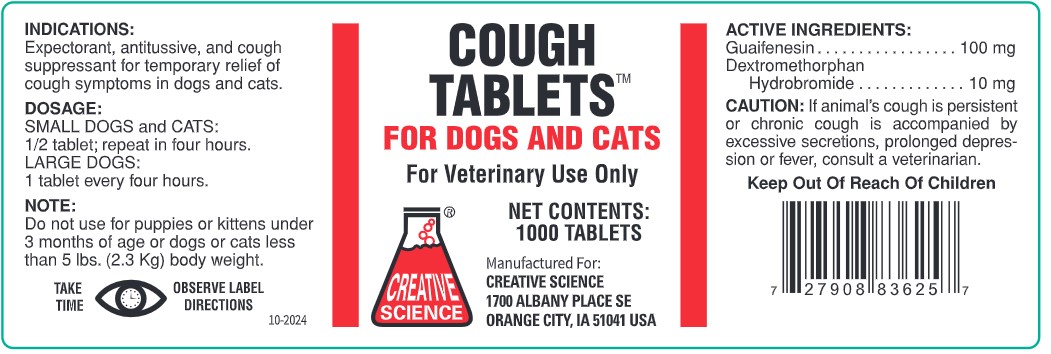 DRUG LABEL: Cough Tabs For Dogs and Cats
NDC: 53413-011 | Form: TABLET
Manufacturer: Creative Science
Category: animal | Type: OTC ANIMAL DRUG LABEL
Date: 20260106

ACTIVE INGREDIENTS: DEXTROMETHORPHAN HYDROBROMIDE 10 mg/1 1; GUAIFENESIN 100 mg/1 1

INDICATIONS:

Expectorant, antitussive, and cough suppressant for temporary relief of cough symptoms in dogs and cats.

DOSAGE:

SMALL DOGS and CATS:

½ tablet; repeat in four hours.

LARGE DOGS:

1 tablet every four hours.

NOTE:

Do not use for puppies or kittens under 3 months of age or dogs or cats less than 5 lbs. (2.3 Kg) body weight.

GENERAL PRECAUTIONS

TAKE TIME... OBSERVE LABEL DIRECTIONS

ACTIVE INGREDIENTS:

Guaifenesin..........................................100 mg

Dextromethorphan Hydrobromide.....10 mg

CAUTION:

If animal's cough is persistent or chronic cough is accompanied by excessive secretions, prolonged depression or fever, consult a veterinarian.

Keep Out Of Reach Of Children

COUGH TABLETS™

FOR DOGS AND CATS

For Veterinary Use Only

NET CONTENTS:

1000 TABLETS

Manufactured For:

CREATIVE SCIENCE

1700 ALBANY PLACE SE

ORANGE CITY, IA 51041 USA